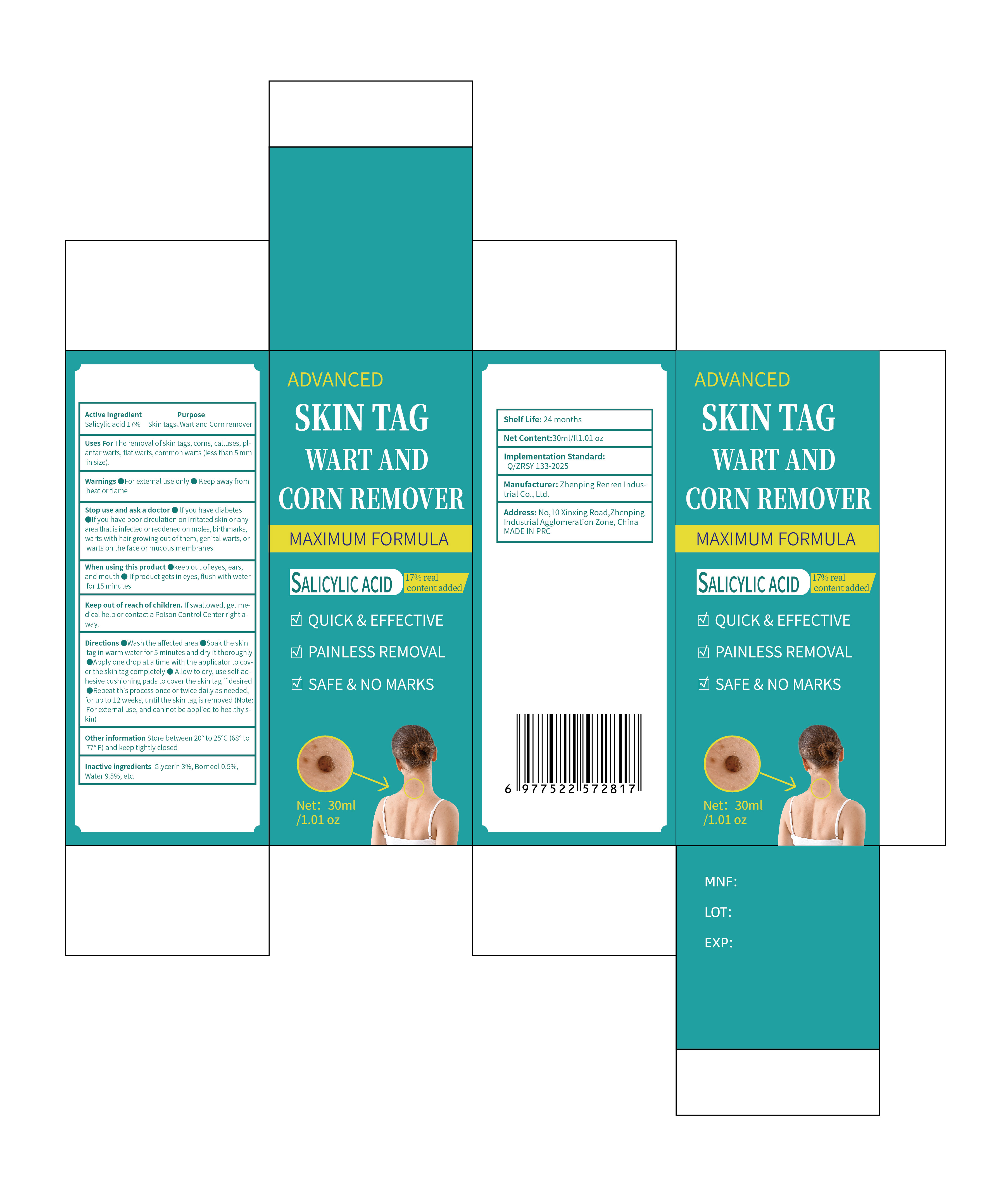 DRUG LABEL: SKIN TAG WART AND CORN REMOVER
NDC: 87096-001 | Form: LIQUID
Manufacturer: Zhenping Renren Industry Co., Ltd.
Category: otc | Type: HUMAN OTC DRUG LABEL
Date: 20250914

ACTIVE INGREDIENTS: SALICYLIC ACID 17 g/100 g
INACTIVE INGREDIENTS: BORNEOL 0.5 g/100 g; WATER 9.5 g/100 g; GLYCERIN 3 g/100 g

Active ingredients

Salicylic acid 17%
Glycerin 3%
Borneol 0.5%
Ethanol 70%
Water 9.5%

Purpose

skin tags、Wart and corn remover

Uses

Uses For The removal of skin tags, corns, calluses, plantar warts, flat warts, common warts (less than 5 mm in size).

Warnings

●For external use only
●Keep away from heat or flame

Stop use and ask a doctor

●If you have diabetes
●If you have poor circulation on irritated skin or any area that is infected or reddened on moles, birthmarks, warts with hair growing out of them, genital warts, or warts on the face or mucous membranes

When using this product

●keep out of eyes, ears, and mouth
●If product gets in eyes, flush with water for 15 minutes

Keep out of reach of children. If swallowed, get medical help or contact a Poison Control Center right away.

Directions

●Wash the affected area
●Soak the skin tag in warm water for 5 minutes and dry it thoroughly
●Apply one drop at a time with the applicator to cover the skin tag completely
●Allow to dry, use self-adhesive cushioning pads to cover the skin tag if desired
●Repeat this process once or twice daily as needed, for up to 12 weeks, until the skin tag is removed (Note: For external use, and can not be applied to healthy skin

Other information

Other information Store between 20° to 25℃ (68° to 77° F) and keep tightly closed

INACTIVE INGREDIENT

Glycerin 3%,Borneol 0.5%, Water 9.5%,etc.

DOSAGE & ADMINISTRATION SECTION

●Wash the affected area
●Soak the skin tag in warm water for 5 minutes and dry it thoroughly
●Apply one drop at a time with the applicator to cover the skin tag completely
●Allow to dry, use self-adhesive cushioning pads to cover the skin tag if desired
●Repeat this process once or twice daily as needed, for up to 12 weeks, until the skin tag is removed (Note: For external use, and can not be applied to healthy skin